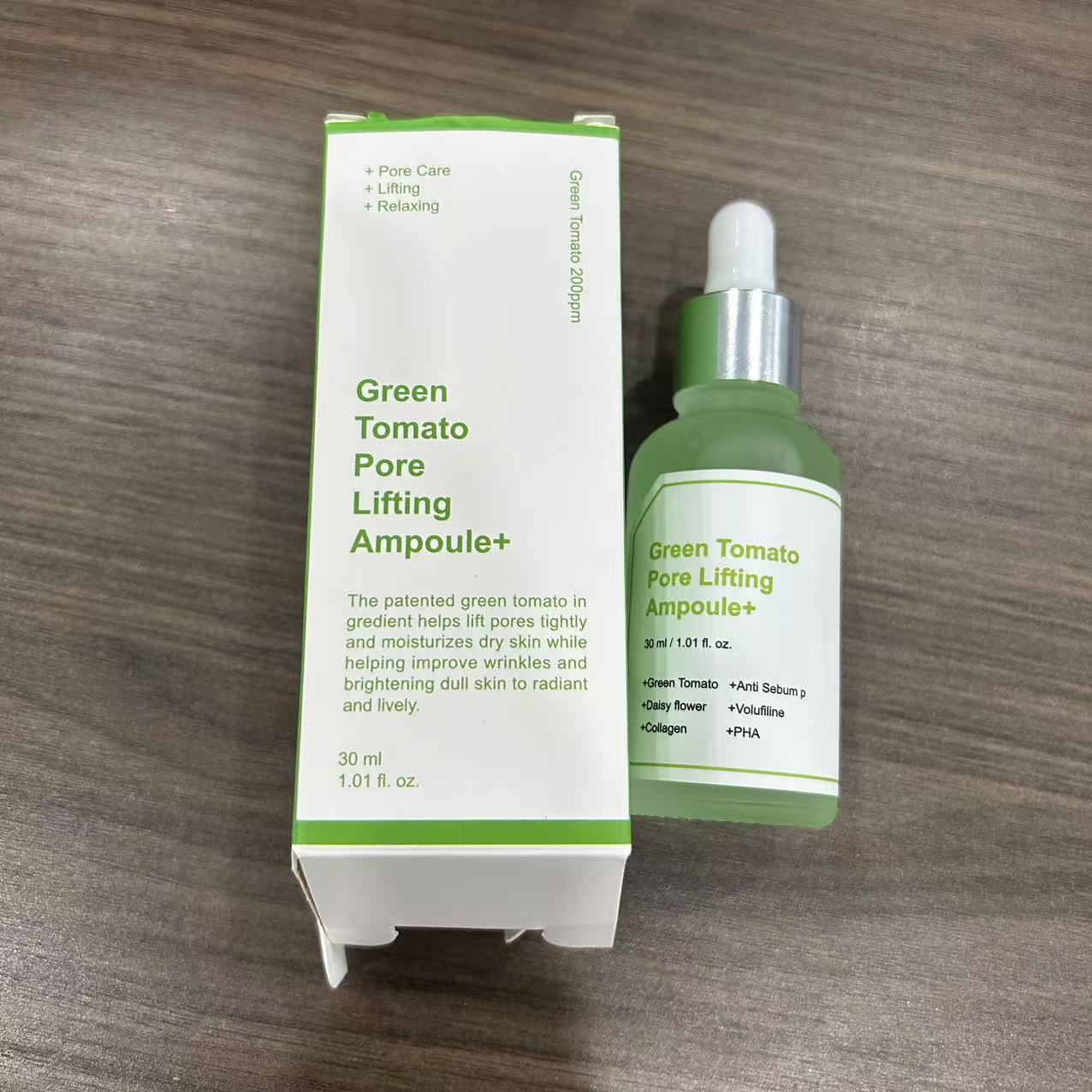 DRUG LABEL: Green Tomato Pore Lifting Ampoule
NDC: 84766-0004 | Form: OIL
Manufacturer: COMFMET LIMITED
Category: otc | Type: HUMAN OTC DRUG LABEL
Date: 20241023

ACTIVE INGREDIENTS: DIACYLGLYCEROL OIL 5 g/100 mL
INACTIVE INGREDIENTS: 2-OCTANOL; 1,2-BUTANEDIOL; HYDROLYZED PORCINE COLLAGEN (ENZYMATIC; 3000 MW); FIBRONECTIN; ACETYL HEXAPEPTIDE-8; SOLANUM LYCOPERSICUM (TOMATO) FRUIT; POLYSORBATE 60; ALLANTOIN; 3-O-ETHYL ASCORBIC ACID; PROPYLENE GLYCOL 1-HEXANOATE; POLYGLUTAMIC ACID (1200 MW); HYDROLYZED PEARL; 1,2-HEXANEDIOL; ELASTIN; SODIUM HYALURONATE; CARBOMER; PEG-40 HYDROGENATED CASTOR OIL; WATER; TRIETHANOLAMINE; AZITHROMYCIN SODIUM DIHYDROGEN PHOSPHATE; DISODIUM PHOSPHATE; ETHYLHEXYLGLYCERIN; HYDROXYETHYL CELLULOSE (100 MPA.S AT 2%); (2-CHLOROPHENYL)METHYL 4-HYDROXYBENZOATE

ACTIVE INGREDIENT

GLYCEROL......5%

PURPOSE

Can lighten hyperpigmentation, whiten, improve skin tone and texture, relieve wrinkles, meticulous care with lotion, refreshing, fast-absorbing, low irritation product

INDICATIONS AND USAGE

Apply one drop on clean skin before your moisturizer and smooth in gently all over face.

WARNINGS

For external use only. Avoid contact with eyes. Keep out of reach of children. Discontinue use in case of irritation.

DO NOT USE

on damaged or broken skin

WHEN USING

FOR EXTERNAL USE ONIY - keep out of eyes. Rinse with water to remove.

STOP USE

lt is recommended to have a skin test (inside the wrist orbehind the ear) before use.If you feel uncomfortable,please stop using it.

ASK DOCTOR

lt is recommended to have a skin test (inside the wrist orbehind the ear) before use.If you feel uncomfortable,please stop using it.

KEEP OUT OF REACH OF CHILDREN

Please place it out of the reach of infants；If swallowed, get medical help or contact a Poison Control Center right away.

INDICATIONS AND USAGE

DIRECTION：
Apply one drop on clean skin before your moisturizer and smooth in gently all over face.
CAUTIONI：
For external use only.

Avoid contact with eyes.

Keep out of reach of children.

Discontinue use in case of irritation.

Please keep it in a cool and dry place and avoid light.

INACTIVE INGREDIENT

Water

propylene glycol

ethylhexylgiycerol

allantoin

sodium hyaluronate

3-o-ethylascorbic acid
hydroxyethyl cellulose

Carbomer

triethanolamine
hydroxybenzoate

PEG-40 hydrogenated castor oil
2-hexanediol

butanediol

octanol

soluble collagen
fibronectin

elastin

acetyihexapepiide-8

polyglutamic acid
Solanum Lyeopersicum(Tomato)Fruit Extract(200ppm)
pearl extract

polysorbate-60

essence

Disodium phosphate
sodium dihydregenphosphate

QUESTIONS

Email:commet515@gmail.com

DOSAGE AND ADMINISTRATION

Please keep it in a cool and dry place and avoid light.